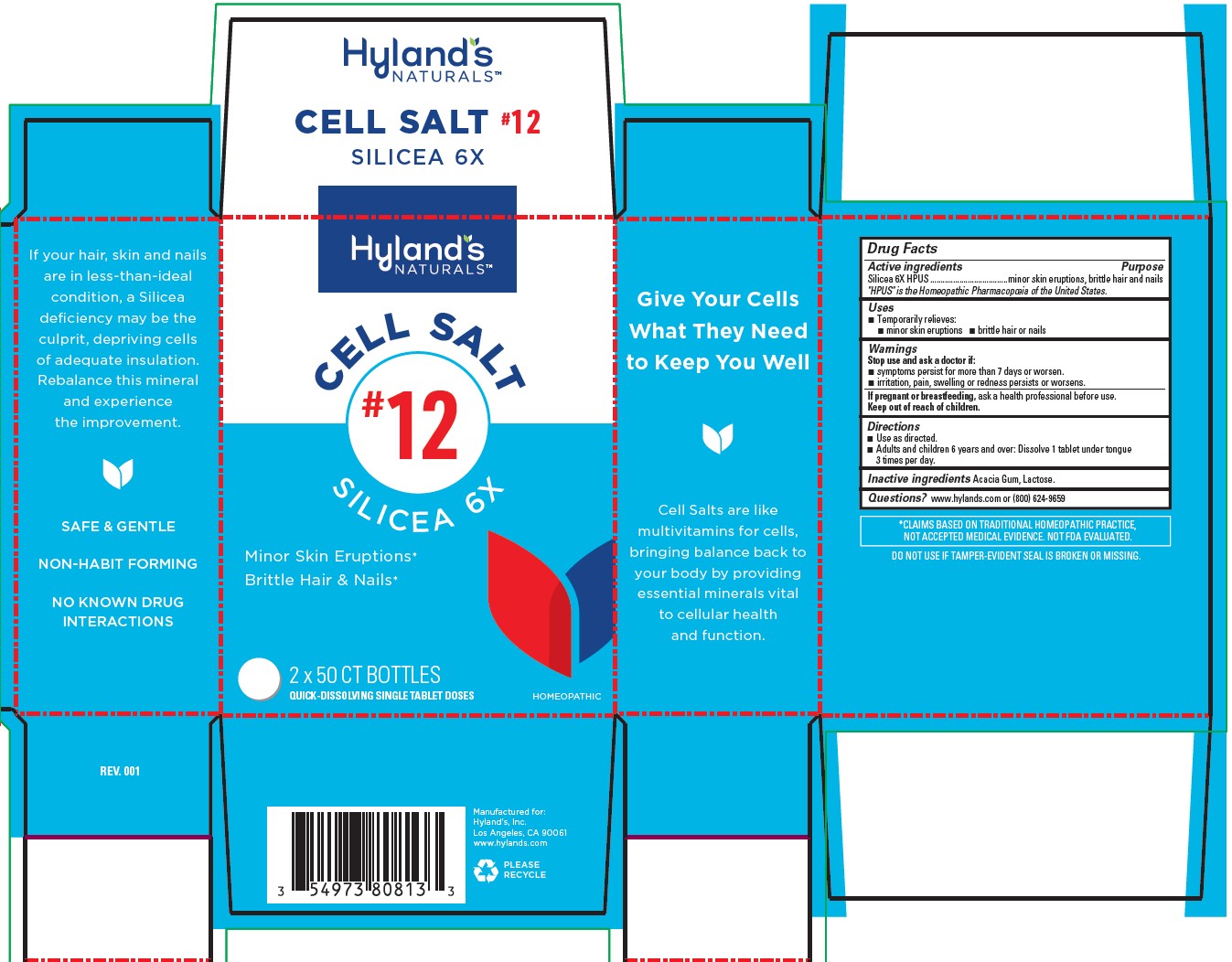 DRUG LABEL: Silicea
NDC: 54973-4083 | Form: TABLET
Manufacturer: Hyland's Inc.
Category: homeopathic | Type: HUMAN OTC DRUG LABEL
Date: 20221214

ACTIVE INGREDIENTS: SILICON DIOXIDE 6 [hp_X]/1 1
INACTIVE INGREDIENTS: ACACIA; LACTOSE MONOHYDRATE

Cell Salt #12 Silicea 6X

PURPOSE

Temporarily relieves minor skin eruptions, brittle hair or nails

Drug Facts

Active ingredients

Active ingredients | Purpose
Silicea 6X HPUS | minor skin eruptions, brittle hair and nails

"HPUS" is the Homeopathic Pharmacopoeia of the United States.

Uses

■ Temporarily relieves:
■ minor skin eruptions ■ brittle hair or nails

Warnings

Stop use and ask a doctor if

■ symptoms persist for more than 7 days or worsen.
■ irritation, pain, swelling or redness persists or worsens.

If pregnant or breastfeeding

ask a health professional before use.

Directions

■ Use as directed.
■ Adults and children 6 years and over: Dissolve 1 tablet under tongue 3 times per day.

Inactive ingredients

Acacia Gum, Lactose.

Questions?

www.hylands.com or (800) 624-9659

PACKAGE LABEL - 2 x 50 TABLETS BOTTLE CARTON

Hyland's

NATURALS™

CELL SALT

#12

SILICEA 6X

Minor Skin Eruptions*

Brittle Hair & Nails*

2x 50 CT BOTTLES

QUICK-DISSOLVING SINGLE TABLET DOSES

HOMEOPATHIC